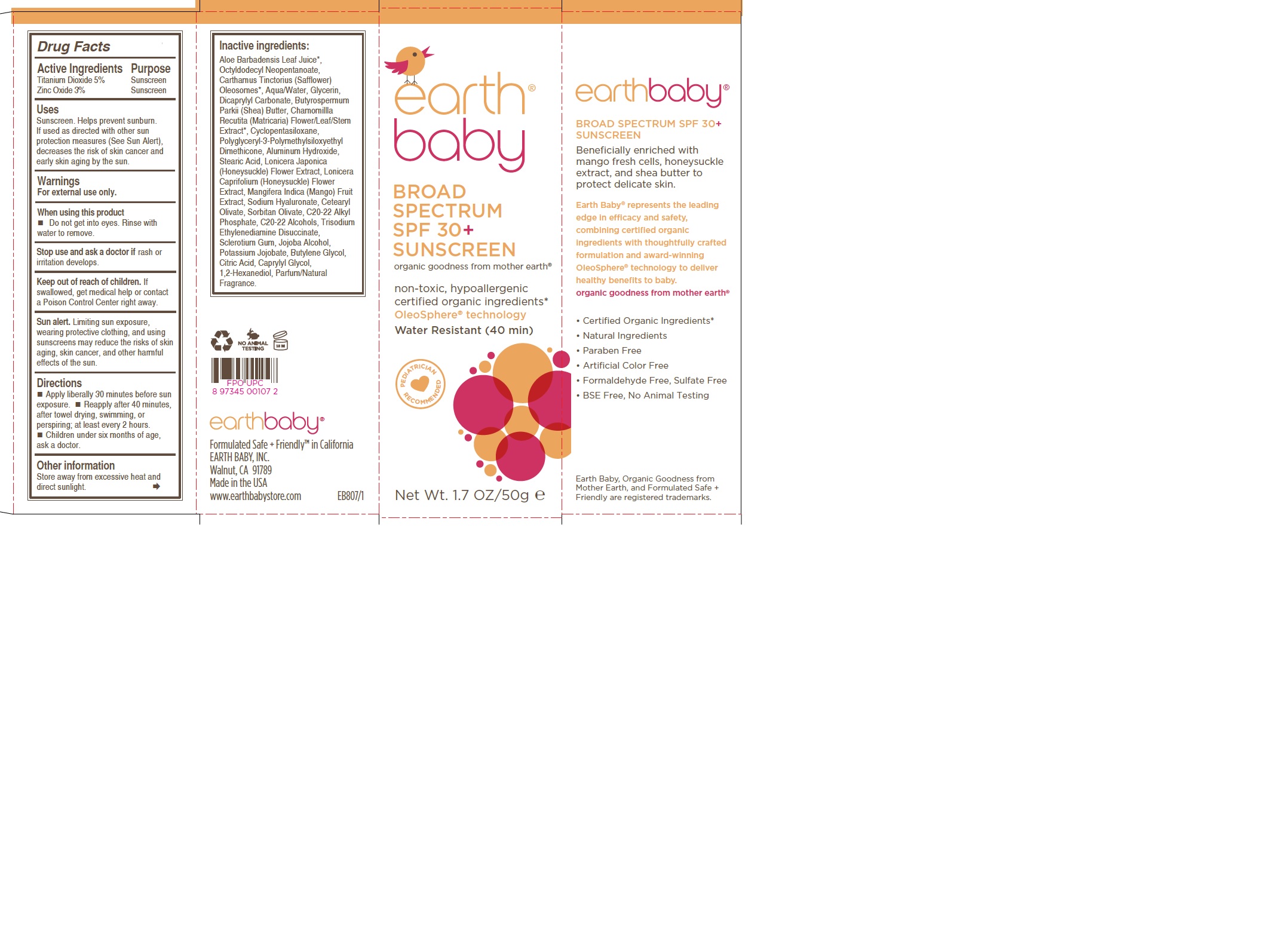 DRUG LABEL: Earth Baby Broad Spectrum SPF 30
NDC: 62588-907 | Form: CREAM
Manufacturer: Earth Baby, Inc.
Category: otc | Type: HUMAN OTC DRUG LABEL
Date: 20250512

ACTIVE INGREDIENTS: ZINC OXIDE 3 g/100 g; TITANIUM DIOXIDE 5 g/100 g
INACTIVE INGREDIENTS: SHEA BUTTER; STEARIC ACID; HYALURONATE SODIUM; CETEARYL OLIVATE; SORBITAN OLIVATE; C20-22 ALKYL PHOSPHATE; GLYCERIN; ALOE; DICAPRYLYL CARBONATE; MANGIFERA INDICA WHOLE; TRISODIUM ETHYLENEDIAMINE DISUCCINATE; BUTYLENE GLYCOL; 1,2-HEXANEDIOL; CARTHAMUS TINCTORIUS (SAFFLOWER) OLEOSOMES; MATRICARIA CHAMOMILLA; ALUMINUM HYDROXIDE; LONICERA JAPONICA FLOWER; LONICERA CAPRIFOLIUM FLOWER; POLYGLYCERYL-3 POLYDIMETHYLSILOXYETHYL DIMETHICONE (4000 MPA.S); C20-22 ALCOHOLS; CAPRYLYL GLYCOL; OCTYLDODECYL NEOPENTANOATE; WATER

Earth Baby Broad Spectrum SPF30+ Sunscreen

ACTIVE INGREDIENT

Titanium Dioxide 5%

Zinc Oxide 3%

PURPOSE

Sunscreen.

WARNINGS

For external use only.

WHEN USING

Do not get into eyes. Rinse with water to remove.

Stop use and ask a doctor if rash or irritation develops.

Keep out of reach of children. If swallowed, get medical help or contact a Poison Control Center right away.

Directions:

Apply liberally 30 minutes before sun exposure.

Reapply after 40 minutes, after towel drying, swimming, or perspiring, atleast every 2 hours.

Children under six months of age, ask a doctor

USER SAFETY WARNINGS

Sun Alert. Limiting sun exposure, wearing protective clothing, and using suncreens may reduce the risks of skin aging, skin cancer, and other harmful effects of the sun.

OTHER SAFETY INFORMATION

Store away from excessive heat and direct sunlight.

INACTIVE INGREDIENT

Aloe Barbadensis Leaf Juice*, Octyldodecyl Neopentanoate, Carthamus Tinctorius (Safflower) Oleosomes*, Aqua/Water, Glycerin, Dicaprylyl Carbonate, Butyrospermum Parkii (Shea) Butter, Chamomillla Recutita (Matricaria) Flower/Leaf/Stem Extract*, Cyclopentasiloxane, Polyglyceryl-3-Polymethylsiloxyethyl Dimethicone, Aluminum Hydroxide, Stearic Acid, Lonicera Japonica (Honeysuckle) Flower Extract, Lonicera Caprifolium (Honeysuckle) Flower Extract, Mangifera Indica (Mango) Fruit Extract, Sodium Hyaluronate, Cetearyl Olivate, Sorbitan Olivate, C20-22 Alkyl Phosphate, C20-22 Alcohols, Trisodium Ethylenediamine Disuccinate, Sclerotium Gum, Jojoba Alcohol, Potassium Jojobate, Butylene Glycol, Citric Acid, Caprylyl Glycol, 1,2-Hexanediol, Parfum/Natural Fragrance.

INDICATIONS AND USAGE

Helps prevent sunburn. If used as directed with other sun protection measures (See Sun Alert), decreases the risk of skin cancer and early skinaging by the sun.